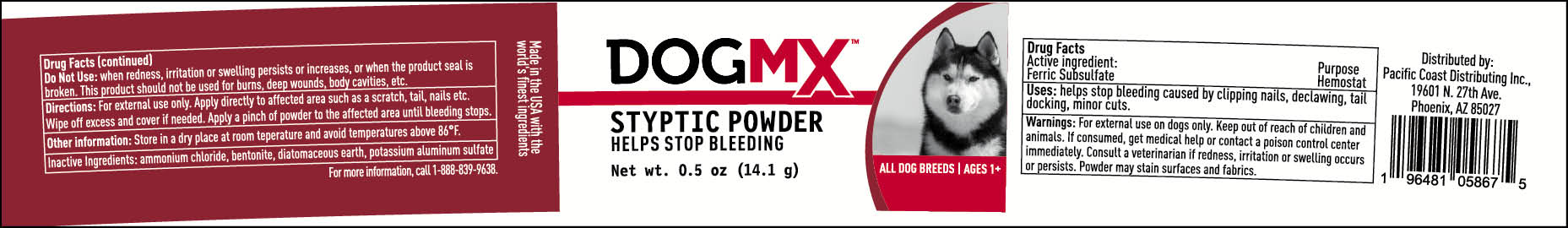 DRUG LABEL: DOG MX STYPTIC
NDC: 86195-867 | Form: POWDER
Manufacturer: TRIDENT SEAFOODS
Category: animal | Type: OTC ANIMAL DRUG LABEL
Date: 20240125

ACTIVE INGREDIENTS: FERRIC SUBSULFATE 1 g/100 g
INACTIVE INGREDIENTS: AMMONIUM CHLORIDE; BENTONITE; DIATOMACEOUS EARTH; POTASSIUM ALUM

DOG MX STYPTIC POWDER 0.5oz

ACTIVE INGREDIENT

FERRIC SUBSULFATE

PURPOSE

HEMOSTAT

WARNINGS

For external use in dogs only. Keep out of reach of children and animals. If consumed, get medical help or contact poison control center immediately. Consult a veterinarian if redness, irriration or swelling occurs or persists. Powder may stain surfaces and fabrics.